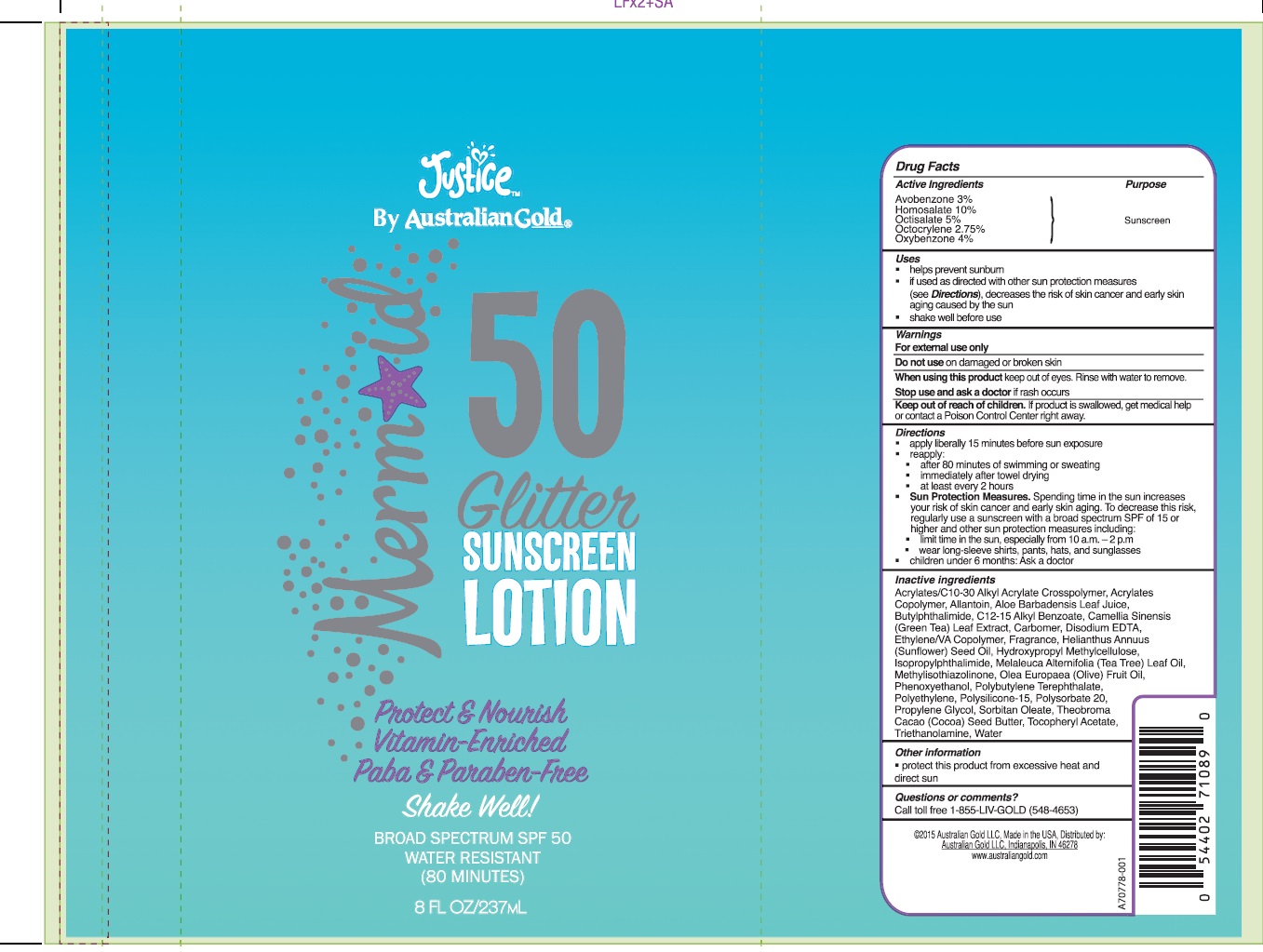 DRUG LABEL: Australian Gold
NDC: 58443-0222 | Form: LOTION
Manufacturer: Prime Enterprises Inc.
Category: otc | Type: HUMAN OTC DRUG LABEL
Date: 20200117

ACTIVE INGREDIENTS: OXYBENZONE 41.04 mg/1 mL; AVOBENZONE 30.78 mg/1 mL; HOMOSALATE 102.6 mg/1 mL; OCTISALATE 51.3 mg/1 mL; OCTOCRYLENE 28.22 mg/1 mL
INACTIVE INGREDIENTS: ETHYLENE-VINYL ACETATE COPOLYMER (50% VINYL ACETATE); GREEN TEA LEAF; TEA TREE OIL; COCOA BUTTER; EDETATE DISODIUM; METHYLISOTHIAZOLINONE; ISOPROPYLPHTHALIMIDE; CARBOMER 940; OLIVE OIL; HIGH DENSITY POLYETHYLENE; POLYSORBATE 20; PROPYLENE GLYCOL; SORBITAN MONOOLEATE; ALKYL (C12-15) BENZOATE; N-BUTYLPHTHALIMIDE; ALOE VERA LEAF; HYPROMELLOSES; (C10-C30)ALKYL METHACRYLATE ESTER; ALPHA-TOCOPHEROL ACETATE; TROLAMINE; WATER; SUNFLOWER OIL; DIMETHYL TEREPHTHALATE; ALLANTOIN; PHENOXYETHANOL; POLYSILICONE-15; METHACRYLIC ACID - ETHYL ACRYLATE COPOLYMER (1:1) TYPE A

Mermaid SPF 50 Glitter Sunscreen

Active Ingredients

Avobenzone 3%

Homosalate 10%

Octisalate 5%

Octocrylene 2.75%

Oxybenzone 4%

Purpose

Sunscreen

Uses

- helps prevent sunburn
- if used as directed with other sun protection measures (see Directions), decreases the risk of skin cancer and early skin aging caused by the sun
- shake well before use

Warnings

For external use only.

Do not use on damaged or broken skin

When using this product keep out of eyes. Rinse with water to remove.

Stop use and ask a doctor if rash occurs

Keep out of reach of children. If product is swallowed, get medical help or contact a Poison Control Center right away.

Directions

- apply liberally 15 minutes before sun exposure
- reapply:
- after 80 minutes of swimming or sweating
- immediately after towel drying
- at least every 2 hours
- Sun Protection Measures. Spending time in the sun increases your risk of skin cancer and early skin aging. To decrease this risk, regularly use a sunscreen with broad spectrum SPF of 15 or higher and other sun protection measures including:
- limit time in the sun, especially from 10 a.m. – 2 p.m.
- wear long-sleeve shirts, pants, hats, and sunglasses
- children under 6 months: Ask a doctor

INACTIVE INGREDIENT

Acrylates/C10-30 Alkyl Acrylate Crosspolymer, Acrylates Copolymer, Allantoin, Aloe Barbadensis Leaf Juice, Butylphthalimide, C12-15 Alkyl Benzoate, Camellia Sinensis (Green Tea) Leaf Extract, Carbomer, Disodium EDTA, Ethylene/VA Copolymer, Fragrance, Helianthus Annuus (Sunflower) Seed Oil, Hydroxypropyl Methylcellulose, Isopropylphthalimide, Melaleuca Alternifolia (Tea Tree) Leaf Oil, Methylisothiazolinone, Olea Europaea (Olive) Fruit Oil, Phenoxyethanol, Polybutylene Terephthalate, Polyethylene, Polysilicone-15, Polysorbate 20, Propylene Glycol, Sorbitan Oleate, Theobroma Cacao (Cocoa) Seed Butter, Tocopheryl Acetate, Triethanolamine, Water

Other Information

- protect this product from excesive heat and direct sun

Questions or comments?

Call toll free 1-855-LIV-GOLD (548-4653)